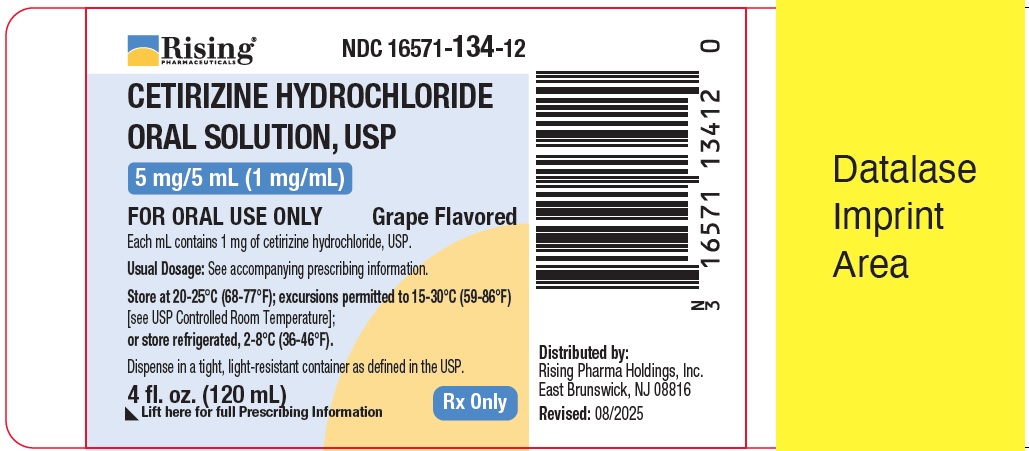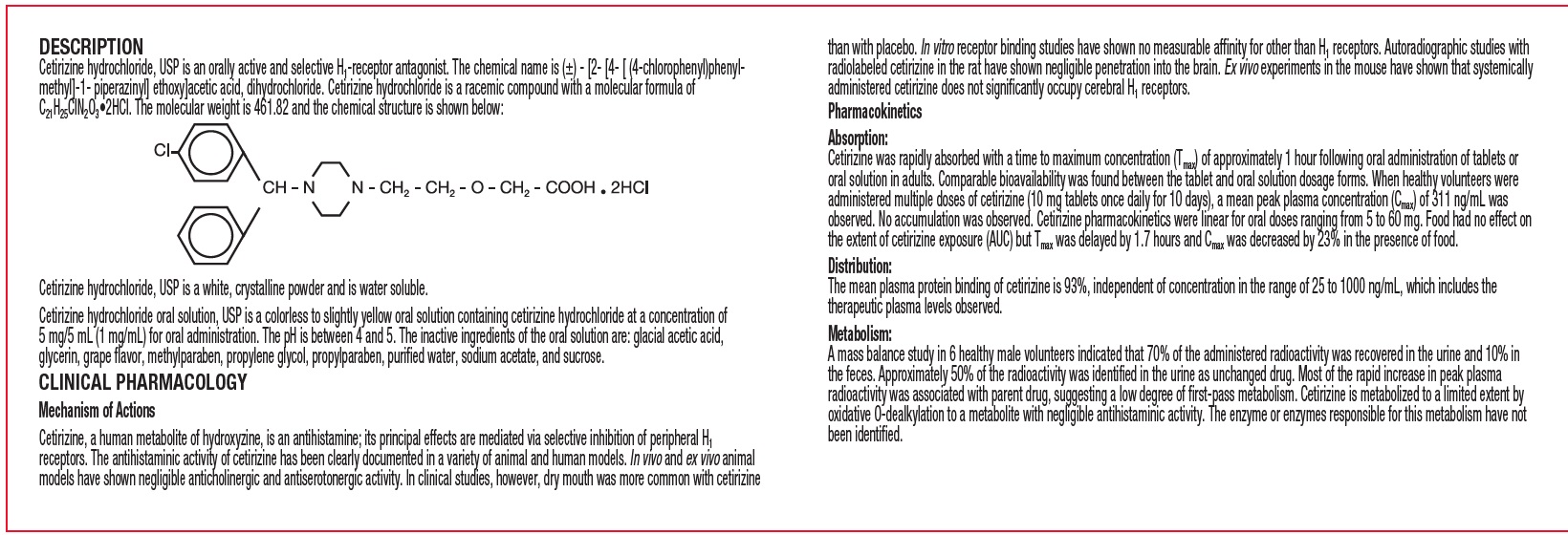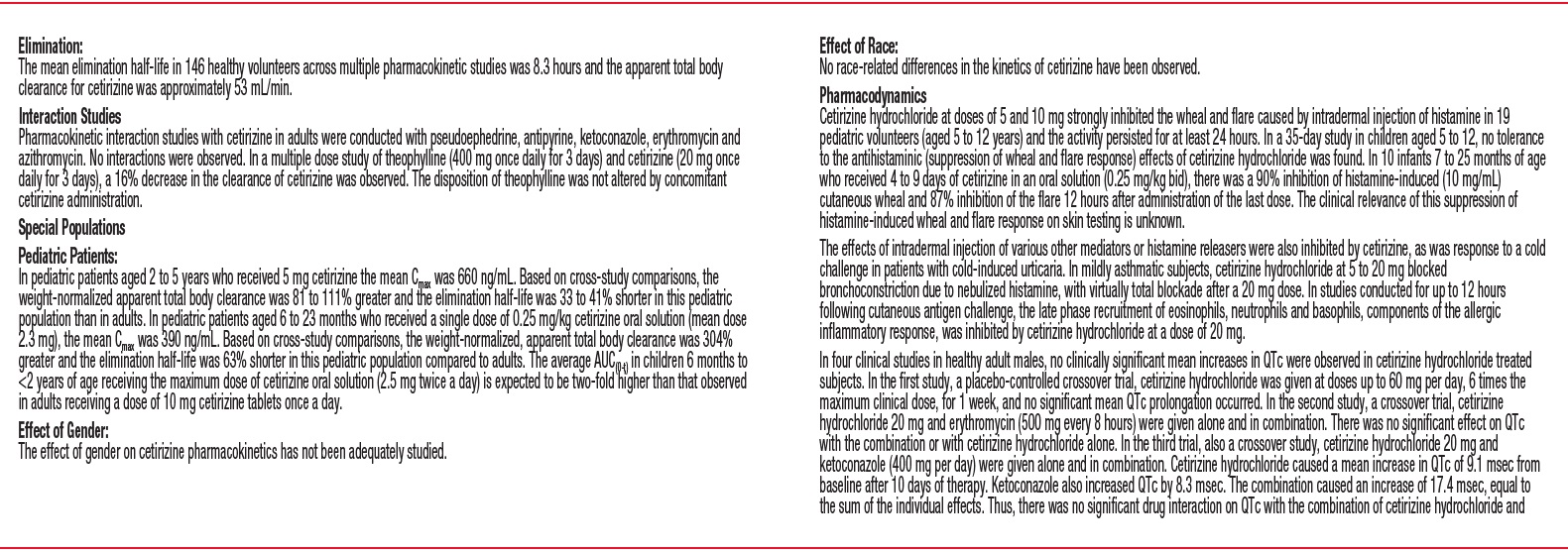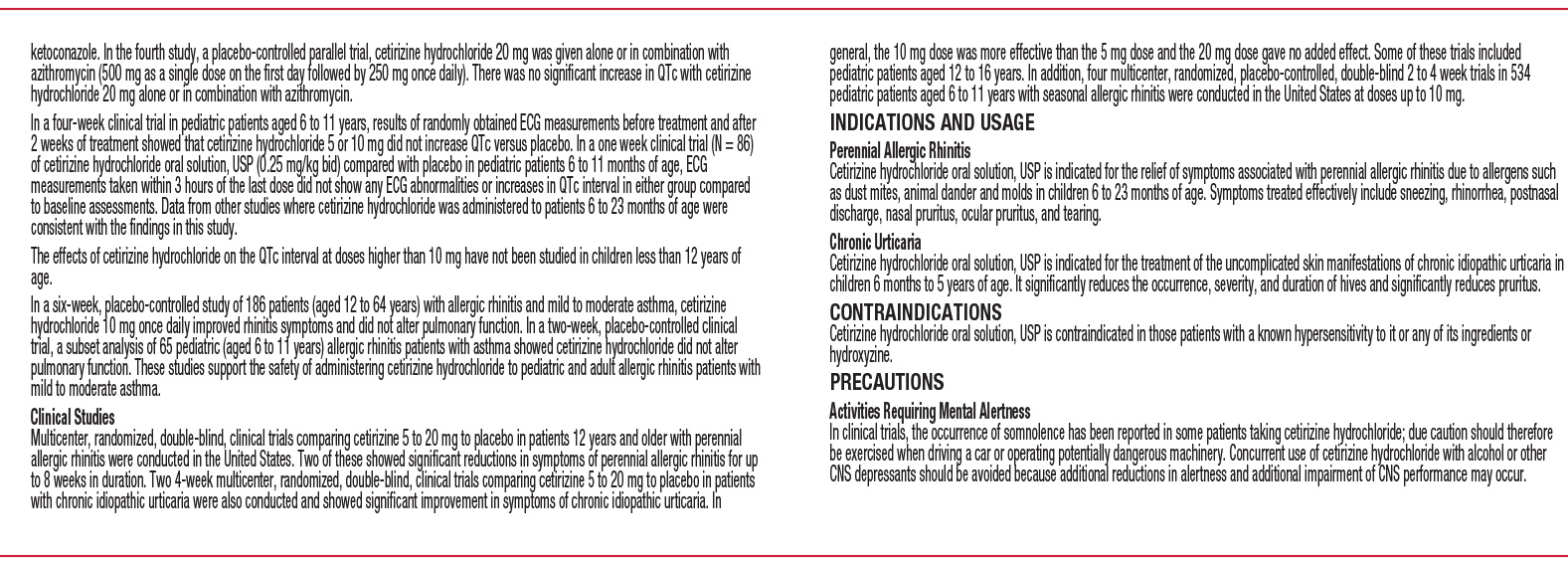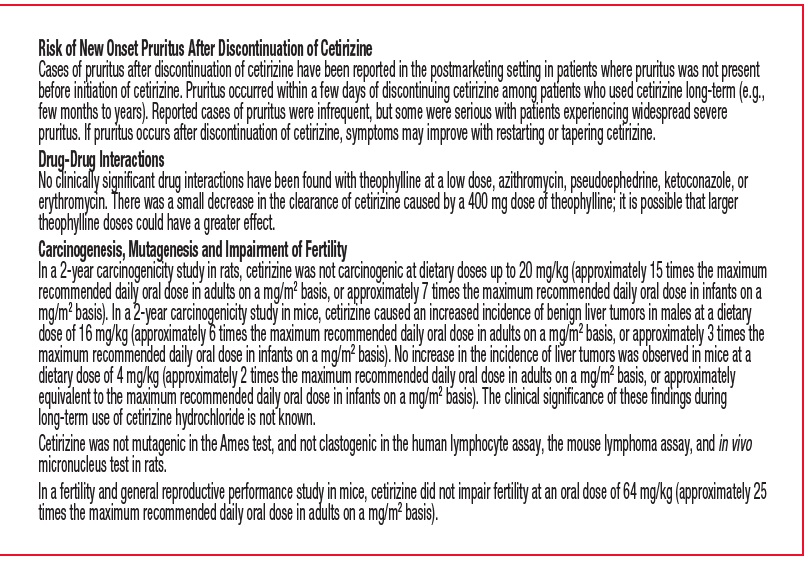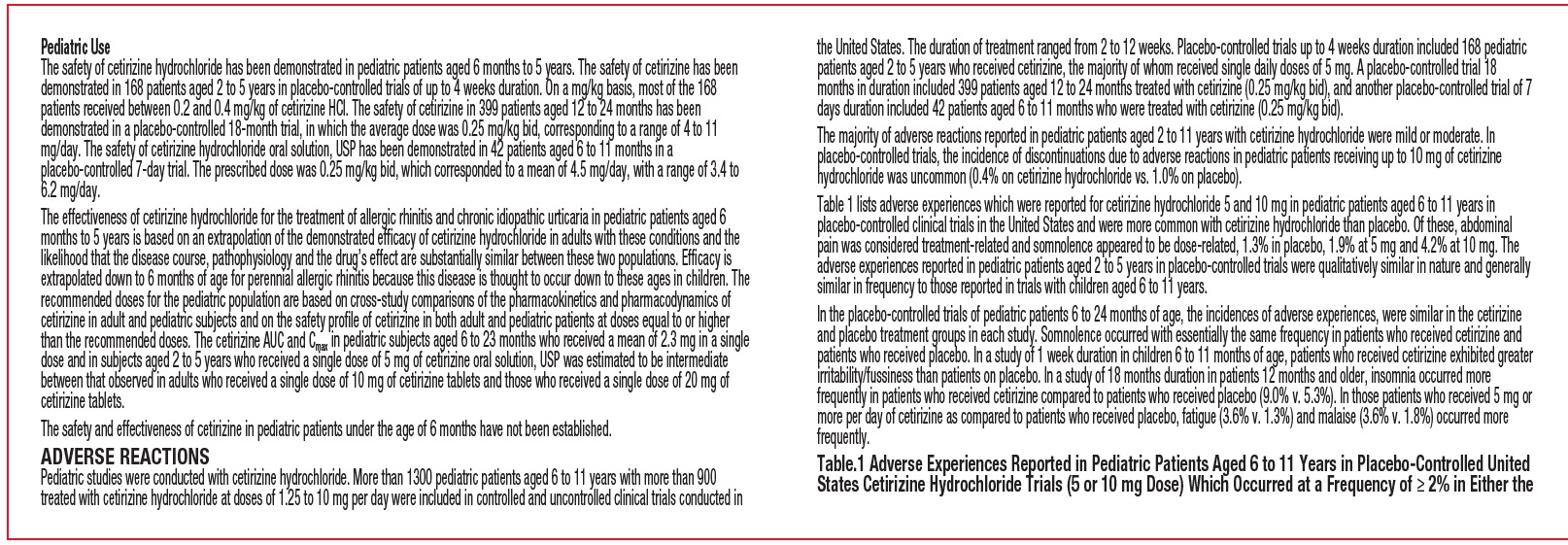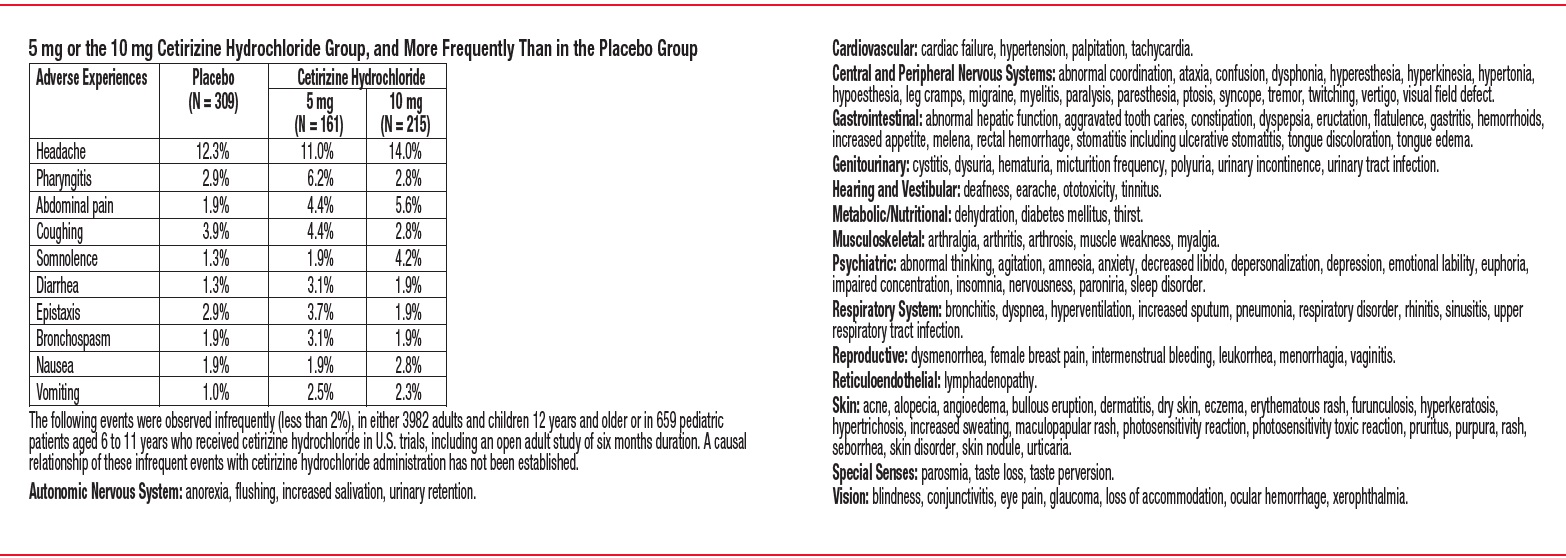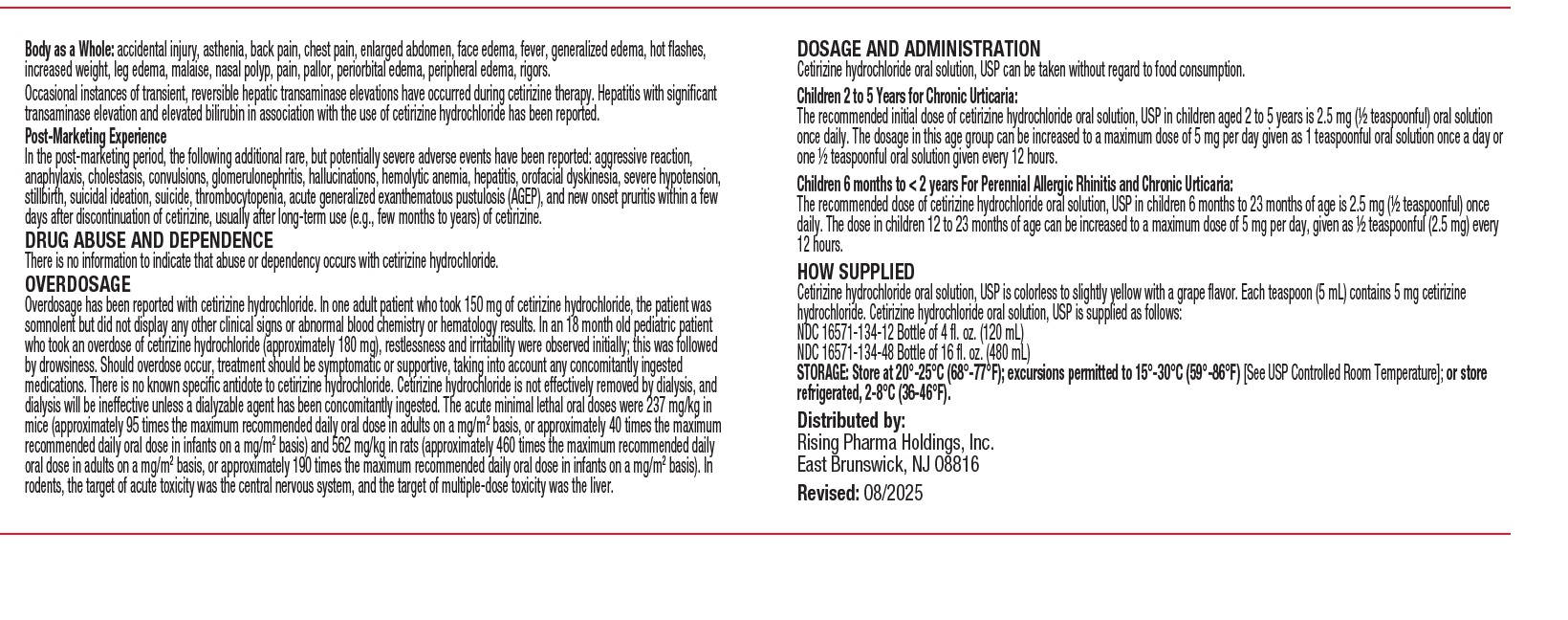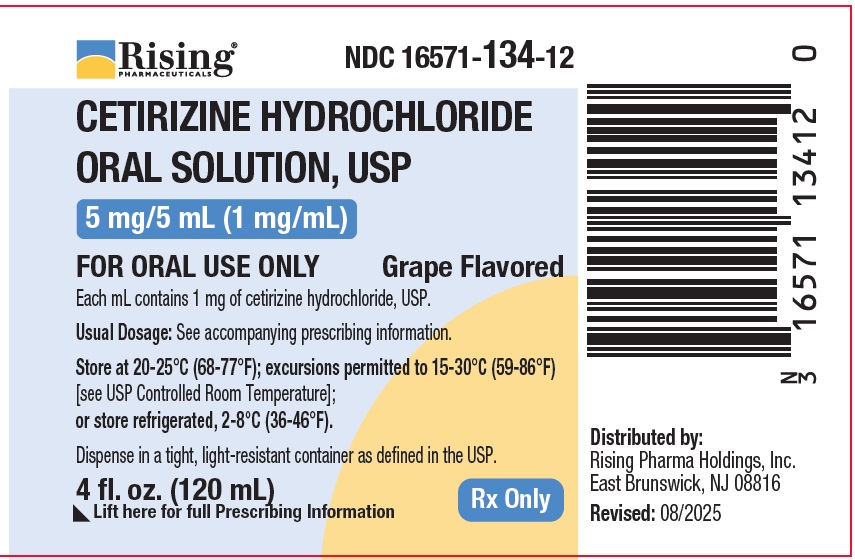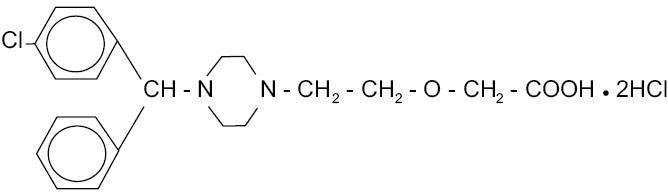 DRUG LABEL: CETIRIZINE HYDROCHLORIDE
NDC: 16571-134 | Form: SOLUTION
Manufacturer: Rising Pharma Holdings, Inc.
Category: prescription | Type: HUMAN PRESCRIPTION DRUG LABEL
Date: 20260113

ACTIVE INGREDIENTS: CETIRIZINE HYDROCHLORIDE 1 mg/1 mL
INACTIVE INGREDIENTS: GLYCERIN; ACETIC ACID; METHYLPARABEN; WATER; PROPYLENE GLYCOL; PROPYLPARABEN; SODIUM ACETATE; SUCROSE

CETIRIZINE HYDROCHLORIDE ORAL SOLUTION, USP
5 mg/5 mL (1 mg/mL)
4 fl. oz. and 16 fl. oz.

DESCRIPTION

Cetirizine hydrochloride, USP is an orally active and selective H 1-receptor antagonist. The chemical name is (±) - [2- [4- [ (4-chlorophenyl)phenylmethyl] -1- piperazinyl] ethoxy]acetic acid, dihydrochloride. Cetirizine hydrochloride is a racemic compound with a molecular formula of C 21H 25ClN 2O 3•2HCl. The molecular weight is 461.82 and the chemical structure is shown below:

Cetirizine hydrochloride, USP is a white, crystalline powder and is water soluble.
Cetirizine hydrochloride oral solution, USP is a colorless to slightly yellow oral solution containing cetirizine hydrochloride at a concentration of 5 mg/5 mL (1 mg/mL) for oral administration. The pH is between 4 and 5. The inactive ingredients of the oral solution are: glacial acetic acid, glycerin, grape flavor, methylparaben, propylene glycol, propylparaben, purified water, sodium acetate, and sucrose.

CLINICAL PHARMACOLOGY

Mechanism of Actions

Cetirizine, a human metabolite of hydroxyzine, is an antihistamine; its principal effects are mediated via selective inhibition of peripheral H1 receptors. The antihistaminic activity of cetirizine has been clearly documented in a variety of animal and human models. In vivo and ex vivo animal models have shown negligible anticholinergic and antiserotonergic activity. In clinical studies, however, dry mouth was more common with cetirizine than with placebo. In vitro receptor binding studies have shown no measurable affinity for other than H1 receptors. Autoradiographic studies with radiolabeled cetirizine in the rat have shown negligible penetration into the brain. Ex vivo experiments in the mouse have shown that systemically administered cetirizine does not significantly occupy cerebral H1 receptors.

Pharmacokinetics

Absorption:

Cetirizine was rapidly absorbed with a time to maximum concentration (Tmax) of approximately 1 hour following oral administration of tablets or oral solution in adults. Comparable bioavailability was found between the tablet and oral solution dosage forms. When healthy volunteers were administered multiple doses of cetirizine (10 mg tablets once daily for 10 days), a mean peak plasma concentration (Cmax) of 311 ng/mL was observed. No accumulation was observed. Cetirizine pharmacokinetics were linear for oral doses ranging from 5 to 60 mg. Food had no effect on the extent of cetirizine exposure (AUC) but Tmax was delayed by 1.7 hours and Cmax was decreased by 23% in the presence of food.

Distribution:

The mean plasma protein binding of cetirizine is 93%, independent of concentration in the range of 25 to 1000 ng/mL, which includes the therapeutic plasma levels observed.

Metabolism:

A mass balance study in 6 healthy male volunteers indicated that 70% of the administered radioactivity was recovered in the urine and 10% in the feces. Approximately 50% of the radioactivity was identified in the urine as unchanged drug. Most of the rapid increase in peak plasma radioactivity was associated with parent drug, suggesting a low degree of first-pass metabolism. Cetirizine is metabolized to a limited extent by oxidative O-dealkylation to a metabolite with negligible antihistaminic activity. The enzyme or enzymes responsible for this metabolism have not been identified.

Elimination:

The mean elimination half-life in 146 healthy volunteers across multiple pharmacokinetic studies was 8.3 hours and the apparent total body clearance for cetirizine was approximately 53 mL/min.

Interaction Studies

Pharmacokinetic interaction studies with cetirizine in adults were conducted with pseudoephedrine, antipyrine, ketoconazole, erythromycin and azithromycin. No interactions were observed. In a multiple dose study of theophylline (400 mg once daily for 3 days) and cetirizine (20 mg once daily for 3 days), a 16% decrease in the clearance of cetirizine was observed. The disposition of theophylline was not altered by concomitant cetirizine administration.

Special Populations

Pediatric Patients:

In pediatric patients aged 2 to 5 years who received 5 mg cetirizine the mean Cmax was 660 ng/mL. Based on cross-study comparisons, the weight-normalized apparent total body clearance was 81 to 111% greater and the elimination half-life was 33 to 41% shorter in this pediatric population than in adults. In pediatric patients aged 6 to 23 months who received a single dose of 0.25 mg/kg cetirizine oral solution (mean dose 2.3 mg), the mean Cmax was 390 ng/mL. Based on cross-study comparisons, the weight-normalized, apparent total body clearance was 304% greater and the elimination half-life was 63% shorter in this pediatric population compared to adults. The average AUC(0-t) in children 6 months to <2 years of age receiving the maximum dose of cetirizine oral solution (2.5 mg twice a day) is expected to be two-fold higher than that observed in adults receiving a dose of 10 mg cetirizine tablets once a day.

Effect of Gender:

The effect of gender on cetirizine pharmacokinetics has not been adequately studied.

Effect of Race:

No race-related differences in the kinetics of cetirizine have been observed.

Pharmacodynamics

Cetirizine hydrochloride at doses of 5 and 10 mg strongly inhibited the wheal and flare caused by intradermal injection of histamine in 19 pediatric volunteers (aged 5 to 12 years) and the activity persisted for at least 24 hours. In a 35-day study in children aged 5 to 12, no tolerance to the antihistaminic (suppression of wheal and flare response) effects of cetirizine hydrochloride was found. In 10 infants 7 to 25 months of age who received 4 to 9 days of cetirizine in an oral solution (0.25 mg/kg bid), there was a 90% inhibition of histamine-induced (10 mg/mL) cutaneous wheal and 87% inhibition of the flare 12 hours after administration of the last dose.

The clinical relevance of this suppression of histamine-induced wheal and flare response on skin testing is unknown.

The effects of intradermal injection of various other mediators or histamine releasers were also inhibited by cetirizine, as was response to a cold challenge in patients with cold-induced urticaria. In mildly asthmatic subjects, cetirizine hydrochloride at 5 to 20 mg blocked bronchoconstriction due to nebulized histamine, with virtually total blockade after a 20 mg dose. In studies conducted for up to 12 hours following cutaneous antigen challenge, the late phase recruitment of eosinophils, neutrophils and basophils, components of the allergic inflammatory response, was inhibited by cetirizine hydrochloride at a dose of 20 mg.

In four clinical studies in healthy adult males, no clinically significant mean increases in QTc were observed in cetirizine hydrochloride treated subjects. In the first study, a placebo-controlled crossover trial, cetirizine hydrochloride was given at doses up to 60 mg per day, 6 times the maximum clinical dose, for 1 week, and no significant mean QTc prolongation occurred. In the second study, a crossover trial, cetirizine hydrochloride 20 mg and erythromycin (500 mg every 8 hours) were given alone and in combination. There was no significant effect on QTc with the combination or with cetirizine hydrochloride alone. In the third trial, also a crossover study, cetirizine hydrochloride 20 mg and ketoconazole (400 mg per day) were given alone and in combination. Cetirizine hydrochloride caused a mean increase in QTc of 9.1 msec from baseline after 10 days of therapy. Ketoconazole also increased QTc by 8.3 msec. The combination caused an increase of 17.4 msec, equal to the sum of the individual effects. Thus, there was no significant drug interaction on QTc with the combination of cetirizine hydrochloride and ketoconazole. In the fourth study, a placebo-controlled parallel trial, cetirizine hydrochloride 20 mg was given alone or in combination with azithromycin (500 mg as a single dose on the first day followed by 250 mg once daily). There was no significant increase in QTc with cetirizine hydrochloride 20 mg alone or in combination with azithromycin.

In a four-week clinical trial in pediatric patients aged 6 to 11 years, results of randomly obtained ECG measurements before treatment and after 2 weeks of treatment showed that cetirizine hydrochloride 5 or 10 mg did not increase QTc versus placebo. In a one week clinical trial (N = 86) of cetirizine hydrochloride oral solution, USP (0.25 mg/kg bid) compared with placebo in pediatric patients 6 to 11 months of age, ECG measurements taken within 3 hours of the last dose did not show any ECG abnormalities or increases in QTc interval in either group compared to baseline assessments. Data from other studies where cetirizine hydrochloride was administered to patients 6 to 23 months of age were consistent with the findings in this study.

The effects of cetirizine hydrochloride on the QTc interval at doses higher than 10 mg have not been studied in children less than 12 years of age.

In a six-week, placebo-controlled study of 186 patients (aged 12 to 64 years) with allergic rhinitis and mild to moderate asthma, cetirizine hydrochloride 10 mg once daily improved rhinitis symptoms and did not alter pulmonary function. In a two-week, placebo-controlled clinical trial, a subset analysis of 65 pediatric (aged 6 to 11 years) allergic rhinitis patients with asthma showed cetirizine hydrochloride did not alter pulmonary function. These studies support the safety of administering cetirizine hydrochloride to pediatric and adult allergic rhinitis patients with mild to moderate asthma.

Clinical Studies

Multicenter, randomized, double-blind, clinical trials comparing cetirizine 5 to 20 mg to placebo in patients 12 years and older with perennial allergic rhinitis were conducted in the United States. Two of these showed significant reductions in symptoms of perennial allergic rhinitis for up to 8 weeks in duration. Two 4-week multicenter, randomized, double-blind, clinical trials comparing cetirizine 5 to 20 mg to placebo in patients with chronic idiopathic urticaria were also conducted and showed significant improvement in symptoms of chronic idiopathic urticaria. In general, the 10 mg dose was more effective than the 5 mg dose and the 20 mg dose gave no added effect. Some of these trials included pediatric patients aged 12 to 16 years. In addition, four multicenter, randomized, placebo-controlled, double-blind 2 to 4 week trials in 534 pediatric patients aged 6 to 11 years with seasonal allergic rhinitis were conducted in the United States at doses up to 10 mg.

INDICATIONS AND USAGE

Perennial Allergic Rhinitis

Cetirizine hydrochloride oral solution, USP is indicated for the relief of symptoms associated with perennial allergic rhinitis due to allergens such as dust mites, animal dander and molds in children 6 to 23 months of age. Symptoms treated effectively include sneezing, rhinorrhea, postnasal discharge, nasal pruritus, ocular pruritus, and tearing.

Chronic Urticaria

Cetirizine hydrochloride oral solution, USP is indicated for the treatment of the uncomplicated skin manifestations of chronic idiopathic urticaria in adults and children 6 months to 5 years of age. It significantly reduces the occurrence, severity, and duration of hives and significantly reduces pruritus.

CONTRAINDICATIONS

Cetirizine hydrochloride oral solution, USP is contraindicated in those patients with a known hypersensitivity to it or any of its ingredients or hydroxyzine.

PRECAUTIONS

Activities Requiring Mental Alertness

In clinical trials, the occurrence of somnolence has been reported in some patients taking cetirizine hydrochloride; due caution should therefore be exercised when driving a car or operating potentially dangerous machinery. Concurrent use of cetirizine hydrochloride with alcohol or other CNS depressants should be avoided because additional reductions in alertness and additional impairment of CNS performance may occur.

Drug-Drug Interactions

No clinically significant drug interactions have been found with theophylline at a low dose, azithromycin, pseudoephedrine, ketoconazole, or erythromycin. There was a small decrease in the clearance of cetirizine caused by a 400 mg dose of theophylline; it is possible that larger theophylline doses could have a greater effect.

Carcinogenesis, Mutagenesis, Impairment of Fertility

In a 2-year carcinogenicity study in rats, cetirizine was not carcinogenic at dietary doses up to 20 mg/kg (approximately 15 times the maximum recommended daily oral dose in adults on a mg/m^2basis, or approximately 7 times the maximum recommended daily oral dose in infants on a mg/m^2 basis). In a 2-year carcinogenicity study in mice, cetirizine caused an increased incidence of benign liver tumors in males at a dietary dose of 16 mg/kg (approximately 6 times the maximum recommended daily oral dose in adults on a mg/m^2 basis, or approximately 3 times the maximum recommended daily oral dose in infants on a mg/m^2 basis). No increase in the incidence of liver tumors was observed in mice at a dietary dose of 4 mg/kg (approximately 2 times the maximum recommended daily oral dose in adults on a mg/m^2 basis, or approximately equivalent to the maximum recommended daily oral dose in infants on a mg/m^2 basis). The clinical significance of these findings during long-term use of cetirizine hydrochloride is not known.

Cetirizine was not mutagenic in the Ames test, and not clastogenic in the human lymphocyte assay, the mouse lymphoma assay, and in vivo micronucleus test in rats.

In a fertility and general reproductive performance study in mice, cetirizine did not impair fertility at an oral dose of 64 mg/kg (approximately 25 times the maximum recommended daily oral dose in adults on a mg/m^2 basis).

Pediatric Use

The safety of cetirizine hydrochloride has been demonstrated in pediatric patients aged 6 months to 5 years. The safety of cetirizine has been demonstrated in 168 patients aged 2 to 5 years in placebo-controlled trials of up to 4 weeks duration. On a mg/kg basis, most of the 168 patients received between 0.2 and 0.4 mg/kg of cetirizine HCl. The safety of cetirizine in 399 patients aged 12 to 24 months has been demonstrated in a placebo-controlled 18-month trial, in which the average dose was 0.25 mg/kg bid, corresponding to a range of 4 to 11 mg/day. The safety of cetirizine hydrochloride oral solution, USP has been demonstrated in 42 patients aged 6 to 11 months in a placebo-controlled 7-day trial. The prescribed dose was 0.25 mg/kg bid, which corresponded to a mean of 4.5 mg/day, with a range of 3.4 to 6.2 mg/day.

The effectiveness of cetirizine hydrochloride for the treatment of allergic rhinitis and chronic idiopathic urticaria in pediatric patients aged 6 months to 5 years is based on an extrapolation of the demonstrated efficacy of cetirizine hydrochloride in adults with these conditions and the likelihood that the disease course, pathophysiology and the drug’s effect are substantially similar between these two populations. Efficacy is extrapolated down to 6 months of age for perennial allergic rhinitis because this disease is thought to occur down to these ages in children. The recommended doses for the pediatric population are based on cross-study comparisons of the pharmacokinetics and pharmacodynamics of cetirizine in adult and pediatric subjects and on the safety profile of cetirizine in both adult and pediatric patients at doses equal to or higher than the recommended doses. The cetirizine AUC and Cmax in pediatric subjects aged 6 to 23 months who received a mean of 2.3 mg in a single dose and in subjects aged 2 to 5 years who received a single dose of 5 mg of cetirizine oral solution, USP was estimated to be intermediate between that observed in adults who received a single dose of 10 mg of cetirizine tablets and those who received a single dose of 20 mg of cetirizine tablets.

The safety and effectiveness of cetirizine in pediatric patients under the age of 6 months have not been established.

ADVERSE REACTIONS

Pediatric studies were conducted with cetirizine hydrochloride. More than 1300 pediatric patients aged 6 to 11 years with more than 900 treated with cetirizine hydrochloride at doses of 1.25 to 10 mg per day were included in controlled and uncontrolled clinical trials conducted in the United States. The duration of treatment ranged from 2 to 12 weeks. Placebo-controlled trials up to 4 weeks duration included 168 pediatric patients aged 2 to 5 years who received cetirizine, the majority of whom received single daily doses of 5 mg.

A placebo-controlled trial 18 months in duration included 399 patients aged 12 to 24 months treated with cetirizine (0.25 mg/kg bid), and another placebo-controlled trial of 7 days duration included 42 patients aged 6 to 11 months who were treated with cetirizine (0.25 mg/kg bid).

The majority of adverse reactions reported in pediatric patients aged 2 to 11 years with cetirizine hydrochloride were mild or moderate. In placebo-controlled trials, the incidence of discontinuations due to adverse reactions in pediatric patients receiving up to 10 mg of cetirizine hydrochloride was uncommon (0.4% on cetirizine hydrochloride vs. 1.0% on placebo).

Table 1 lists adverse experiences which were reported for cetirizine hydrochloride 5 and 10 mg in pediatric patients aged 6 to 11 years in placebo-controlled clinical trials in the United States and were more common with cetirizine hydrochloride than placebo. Of these, abdominal pain was considered treatment-related and somnolence appeared to be dose-related, 1.3% in placebo, 1.9% at 5 mg and 4.2% at 10 mg. The adverse experiences reported in pediatric patients aged 2 to 5 years in placebo-controlled trials were qualitatively similar in nature and generally similar in frequency to those reported in trials with children aged 6 to 11 years.

In the placebo-controlled trials of pediatric patients 6 to 24 months of age, the incidences of adverse experiences, were similar in the cetirizine and placebo treatment groups in each study. Somnolence occurred with essentially the same frequency in patients who received cetirizine and patients who received placebo. In a study of 1 week duration in children 6 to 11 months of age, patients who received cetirizine exhibited greater irritability/fussiness than patients on placebo. In a study of 18 months duration in patients 12 months and older, insomnia occurred more frequently in patients who received cetirizine compared to patients who received placebo (9.0% v. 5.3%). In those patients who received 5 mg or more per day of cetirizine as compared to patients who received placebo, fatigue (3.6% v. 1.3%) and malaise (3.6% v. 1.8%) occurred more frequently.

Table.1 Adverse Experiences Reported in Pediatric Patients Aged 6 to 11 Years in Placebo-Controlled United States Cetirizine Hydrochloride Trials (5 or 10 mg Dose) Which Occurred at a Frequency of ≥ 2% in Either the 5 mg or the 10 mg Cetirizine Hydrochloride Group, and More Frequently Than in the Placebo Group
Adverse Experiences |  | Cetirizine Hydrochloride
 | Placebo (N = 309) | 5 mg (N = 161) | 10 mg (N = 215)
Headache | 12.3% | 11.0% | 14.0%
Pharyngitis | 2.9% | 6.2% | 2.8%
Abdominal pain | 1.9% | 4.4% | 5.6%
Coughing | 3.9% | 4.4% | 2.8%
Somnolence | 1.3% | 1.9% | 4.2%
Diarrhea | 1.3% | 3.1% | 1.9%
Epistaxis | 2.9% | 3.7% | 1.9%
Bronchospasm | 1.9% | 3.1% | 1.9%
Nausea | 1.9% | 1.9% | 2.8%
Vomiting | 1.0% | 2.5% | 2.3%

The following events were observed infrequently (less than 2%), in either 3982 adults and children 12 years and older or in 659 pediatric patients aged 6 to 11 years who received cetirizine hydrochloride in U.S. trials, including an open adult study of six months duration. A causal relationship of these infrequent events with cetirizine hydrochloride administration has not been established.

Autonomic Nervous System: anorexia, flushing, increased salivation, urinary retention.

Cardiovascular: cardiac failure, hypertension, palpitation, tachycardia.

Central and Peripheral Nervous Systems: abnormal coordination, ataxia, confusion, dysphonia, hyperesthesia, hyperkinesia, hypertonia, hypoesthesia, leg cramps, migraine, myelitis, paralysis, paresthesia, ptosis, syncope, tremor, twitching, vertigo, visual field defect.

Gastrointestinal: abnormal hepatic function, aggravated tooth caries, constipation, dyspepsia, eructation, flatulence, gastritis, hemorrhoids, increased appetite, melena, rectal hemorrhage, stomatitis including ulcerative stomatitis, tongue discoloration, tongue edema.

Genitourinary: cystitis, dysuria, hematuria, micturition frequency, polyuria, urinary incontinence, urinary tract infection.

Hearing and Vestibular: deafness, earache, ototoxicity, tinnitus.

Metabolic/Nutritional: dehydration, diabetes mellitus, thirst.

Musculoskeletal: arthralgia, arthritis, arthrosis, muscle weakness, myalgia.

Psychiatric: abnormal thinking, agitation, amnesia, anxiety, decreased libido, depersonalization, depression, emotional lability, euphoria, impaired concentration, insomnia, nervousness, paroniria, sleep disorder.

Respiratory System: bronchitis, dyspnea, hyperventilation, increased sputum, pneumonia, respiratory disorder, rhinitis, sinusitis, upper respiratory tract infection.

Reproductive: dysmenorrhea, female breast pain, intermenstrual bleeding, leukorrhea, menorrhagia, vaginitis.

Reticuloendothelial: lymphadenopathy.

Skin: acne, alopecia, angioedema, bullous eruption, dermatitis, dry skin, eczema, erythematous rash, furunculosis, hyperkeratosis, hypertrichosis, increased sweating, maculopapular rash, photosensitivity reaction, photosensitivity toxic reaction, pruritus, purpura, rash, seborrhea, skin disorder, skin nodule, urticaria.

Special Senses: parosmia, taste loss, taste perversion.

Vision: blindness, conjunctivitis, eye pain, glaucoma, loss of accommodation, ocular hemorrhage, xerophthalmia.

Body as a Whole: accidental injury, asthenia, back pain, chest pain, enlarged abdomen, face edema, fever, generalized edema, hot flashes, increased weight, leg edema, malaise, nasal polyp, pain, pallor, periorbital edema, peripheral edema, rigors. Occasional instances of transient, reversible hepatic transaminase elevations have occurred during cetirizine therapy. Hepatitis with significant transaminase elevation and elevated bilirubin in association with the use of cetirizine hydrochloride has been reported.

Post-Marketing Experience

In the post-marketing period, the following additional rare, but potentially severe adverse events have been reported: aggressive reaction,
anaphylaxis, cholestasis, convulsions, glomerulonephritis, hallucinations, hemolytic anemia, hepatitis, orofacial dyskinesia, severe hypotension,
stillbirth, suicidal ideation, suicide, thrombocytopenia, acute generalized exanthematous pustulosis (AGEP), and new onset pruritis within a few
days after discontinuation of cetirizine, usually after long-term use (e.g., few months to years) of cetirizine.

DRUG ABUSE AND DEPENDENCE

There is no information to indicate that abuse or dependency occurs with cetirizine hydrochloride.

OVERDOSAGE

Overdosage has been reported with cetirizine hydrochloride. In one adult patient who took 150 mg of cetirizine hydrochloride, the patient was somnolent but did not display any other clinical signs or abnormal blood chemistry or hematology results. In an 18 month old pediatric patient who took an overdose of cetirizine hydrochloride (approximately 180 mg), restlessness and irritability were observed initially; this was followed by drowsiness. Should overdose occur, treatment should be symptomatic or supportive, taking into account any concomitantly ingested medications. There is no known specific antidote to cetirizine hydrochloride. Cetirizine hydrochloride is not effectively removed by dialysis, and dialysis will be ineffective unless a dialyzable agent has been concomitantly ingested. The acute minimal lethal oral doses were 237 mg/kg in mice (approximately 95 times the maximum recommended daily oral dose in adults on a mg/m^2 basis, or approximately 40 times the maximum recommended daily oral dose in infants on a mg/m^2 basis) and 562 mg/kg in rats (approximately 460 times the maximum recommended daily oral dose in adults on a mg/m^2 basis, or approximately 190 times the maximum recommended daily oral dose in infants on a mg/m^2 basis). In rodents, the target of acute toxicity was the central nervous system, and the target of multiple-dose toxicity was the liver.

DOSAGE AND ADMINISTRATION

Cetirizine hydrochloride oral solution, USP can be taken without regard to food consumption.

Children 2 to 5 Years for Chronic Urticaria:

The recommended initial dose of cetirizine hydrochloride oral solution, USP in children aged 2 to 5 years is 2.5 mg (½ teaspoonful) oral solution once daily. The dosage in this age group can be increased to a maximum dose of 5 mg per day given as 1 teaspoonful oral solution once a day or one ½ teaspoonful oral solution given every 12 hours.

Children 6 months to < 2 years For Perennial Allergic Rhinitis and Chronic Urticaria:

The recommended dose of cetirizine hydrochloride oral solution, USP in children 6 months to 23 months of age is 2.5 mg (½ teaspoonful) once daily. The dose in children 12 to 23 months of age can be increased to a maximum dose of 5 mg per day, given as ½ teaspoonful (2.5 mg) every 12 hours.

HOW SUPPLIED

Cetirizine hydrochloride oral solution, USP is colorless to slightly yellow with a grape flavor. Each teaspoon (5 mL) contains 5 mg cetirizine hydrochloride. Cetirizine hydrochloride oral solution, USP is supplied as follows:

NDC 16571-134-12 Bottle of 4 fl. oz. (120 mL)
NDC 16571-134-48 Bottle of 16 fl. oz. (480 mL)

STORAGE: Store at 20°-25°C (68°-77°F); excursions permitted to 15°-30°C (59°-86°F) [See USP Controlled Room Temperature]; or store refrigerated, 2-8°C (36-46°F).

Distributed by:
Rising Pharma Holdings, Inc.
East Brunswick, NJ 08816

Revised: 08/2025

PACKAGE LABEL.PRINCIPAL DISPLAY PANEL - 120 mL

NDC 16571-134-12

CETIRIZINE HYDROCHLORIDE

ORAL SOLUTION, USP

1 mg/mL (5 mg/5 mL)

FOR ORAL USE ONLY

Grape Flavored

Rx Only

4 fl.oz. (120 mL)